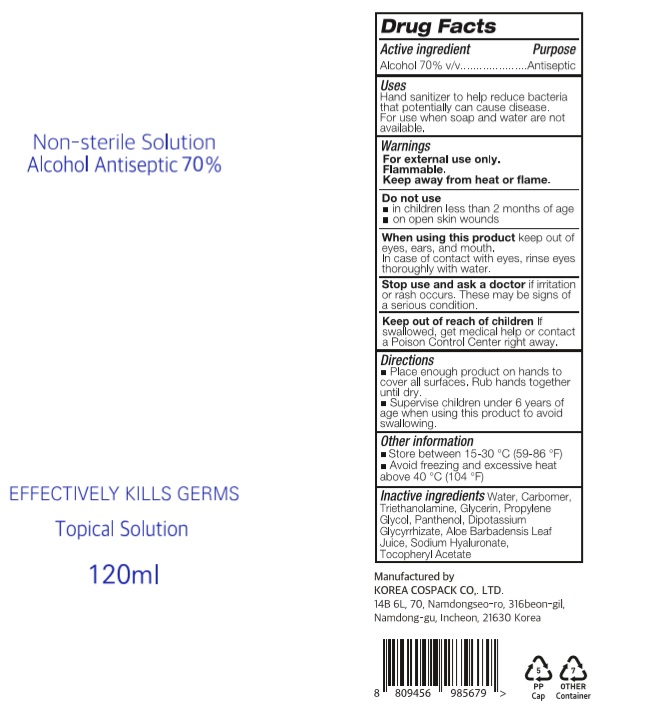 DRUG LABEL: CLEAN TO CLEAN HAND SANITIZER Gel PLUS
NDC: 74064-1271 | Form: GEL
Manufacturer: KOREA COSPACK CO.,LTD.
Category: otc | Type: HUMAN OTC DRUG LABEL
Date: 20200526

ACTIVE INGREDIENTS: ALCOHOL 84 mL/120 mL
INACTIVE INGREDIENTS: GLYCERIN; CARBOMER HOMOPOLYMER, UNSPECIFIED TYPE; WATER; PROPYLENE GLYCOL; PANTHENOL; GLYCYRRHIZINATE DIPOTASSIUM; ALOE VERA LEAF; .ALPHA.-TOCOPHEROL ACETATE; HYALURONATE SODIUM; TROLAMINE

CLEAN TO CLEAN HAND SANITIZER GEL PLUS 120ml, TUBE
74064-1271-1